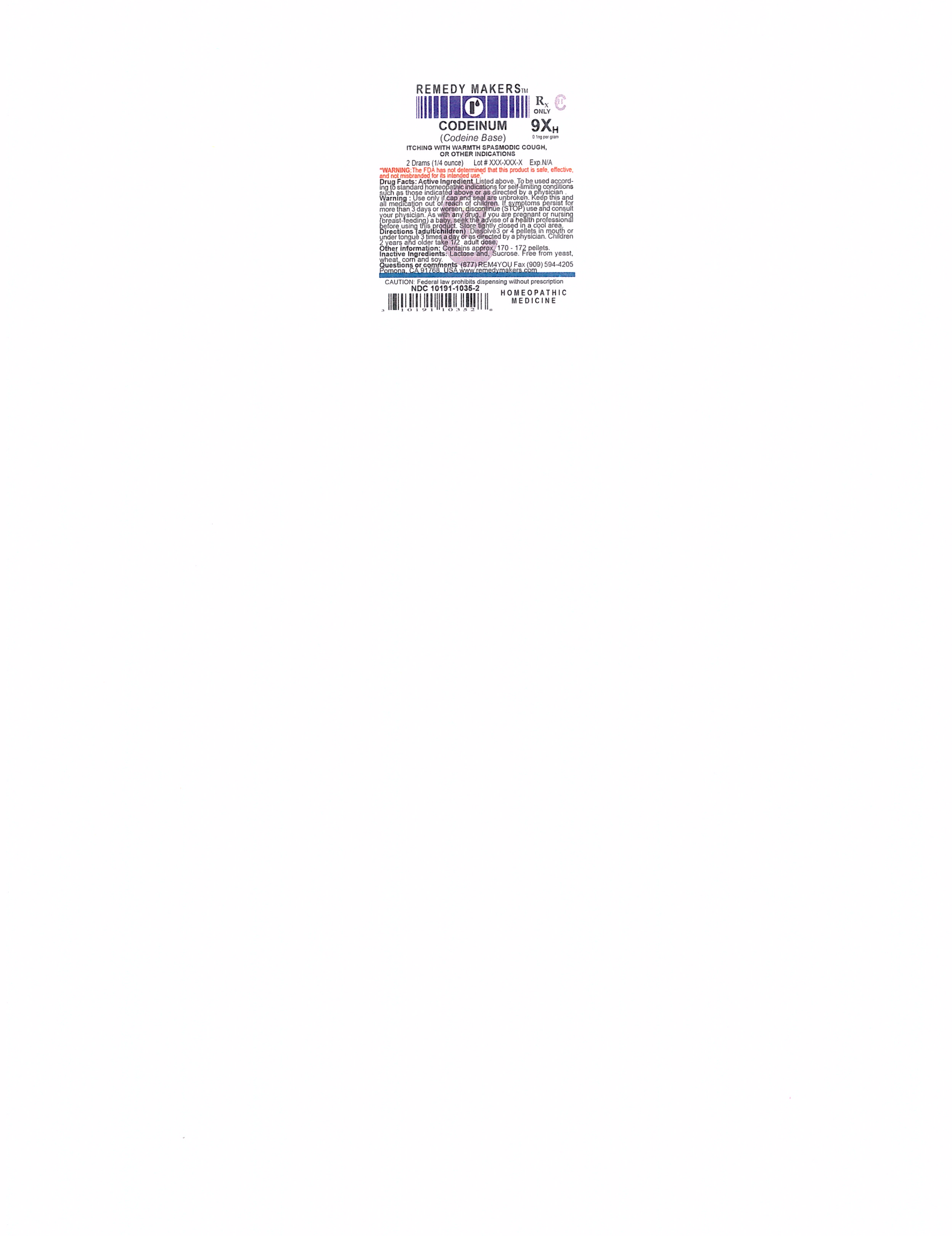 DRUG LABEL: CODEINUM
NDC: 10191-1035 | Form: PELLET
Manufacturer: Remedy Makers
Category: homeopathic | Type: HUMAN PRESCRIPTION DRUG LABEL
Date: 20230307
DEA Schedule: CII

ACTIVE INGREDIENTS: CODEINE ANHYDROUS 9 [hp_X]/1 1
INACTIVE INGREDIENTS: SUCROSE; LACTOSE

CII

WARNING

"The FDA has not determined that the product is safe, effective and not misbranded for its intended use"

INDICATION:

VERTIGO, DIARRHEA, PAIN OR OTHER INDICATIONS

WARNING:

Use only if cap and seal are unbroken. Keep this and all medication out of reach of children. If symptoms persist for more than 3 days or worsen, discontinue (STOP) use and consult your physician. As with any drug. If you are pregnant or nursing (breast-feeding) a baby, seek the advise of a health professional before using this product. Store tightly closed in a cool area.

Directions (adult/children)

Dissolve 3 or 4 pellets in mouth or under tongue 3 times a day or as directed by a physician. Children 2 years and older take 1/2 adult dose.

Inactive Ingredients

Lactose and Sucrose. Free from yeast, wheat, corn and soy.

Other Information

Contains approx. 170 - 172 pellets.

Questions or comments:

(877) REM4YOU Fax (909) 594-4205 Pomona, Ca. 91768 USA www.remedymakers.com

WARNINGS AND PRECAUTIONS

CAUTION: Federal law prohibits dispensing withhout prescription.